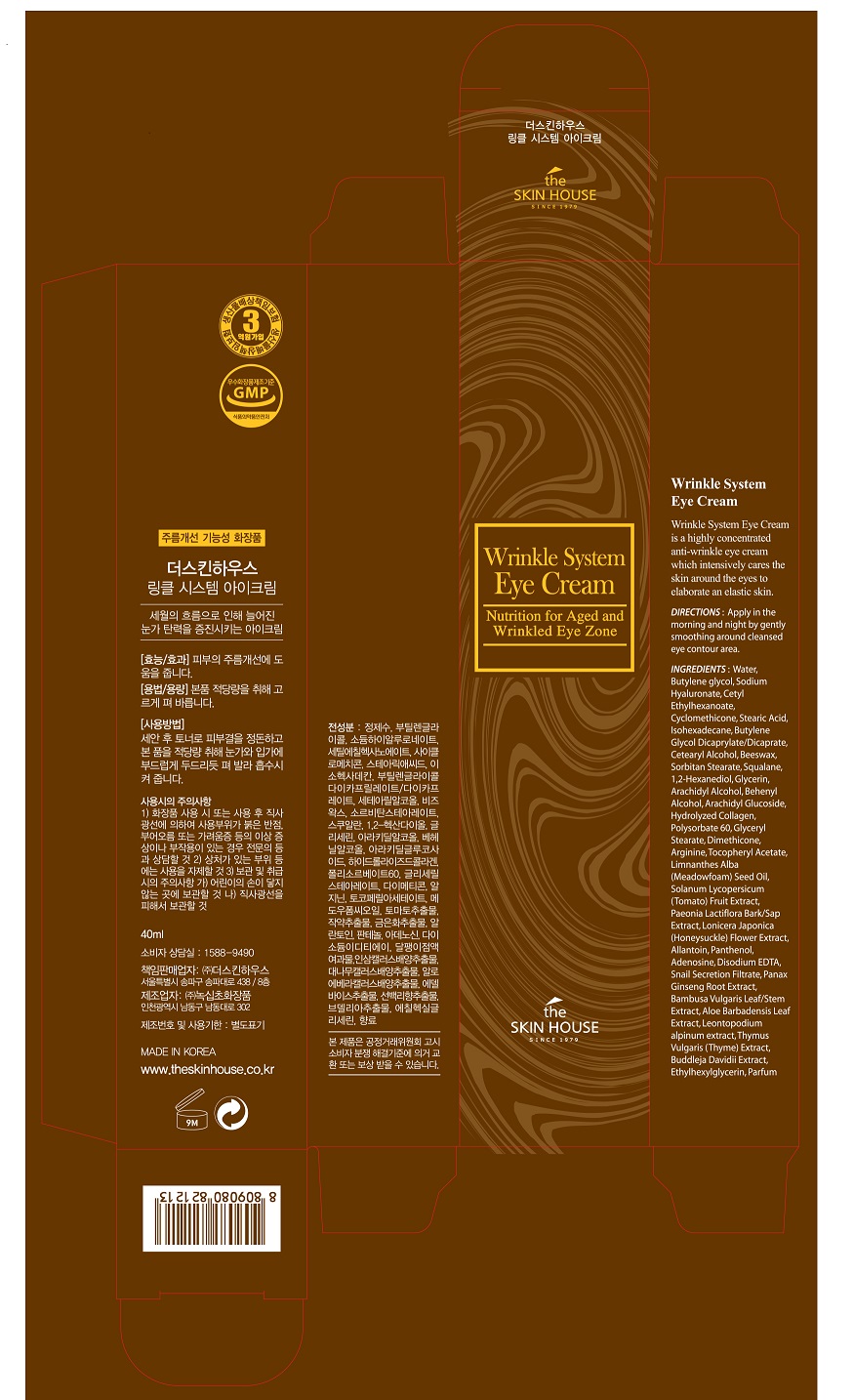 DRUG LABEL: THE SKIN HOUSE Wrinkle System EyeCream
NDC: 73590-0035 | Form: CREAM
Manufacturer: NOKSIBCHO cosmetic Co., Ltd.
Category: otc | Type: HUMAN OTC DRUG LABEL
Date: 20200331

ACTIVE INGREDIENTS: ADENOSINE 0.04 g/100 mL
INACTIVE INGREDIENTS: WATER

Drug Facts

ACTIVE INGREDIENT

adenosine

INACTIVE INGREDIENT

Water
Butylene glycol
Sodium Hyaluronate
Cetyl Ethylhexanoate
Cyclomethicone
Stearic Acid
Isohexadecane
Butylene Glycol Dicaprylate/Dicaprate
Cetearyl Alcohol
Beeswax
Sorbitan Stearate
Squalane
1,2-Hexanediol
Glycerin
Arachidyl Alcohol
Behenyl Alcohol
Arachidyl Glucoside
Hydrolyzed Collagen
Polysorbate 60
Glyceryl Stearate
Dimethicone
Arginine
Tocopheryl Acetate
Limnanthes Alba (Meadowfoam) Seed Oil
Solanum Lycopersicum (Tomato) Fruit Extract
Paeonia Lactiflora Bark/Sap Extract
Lonicera Japonica (Honeysuckle) Flower Extract
Allantoin
Panthenol
Disodium EDTA
Snail Secretion Filtrate
Panax Ginseng Root Extract
Bambusa Vulgaris Leaf/Stem Extract
Aloe Barbadensis Leaf Extract
Leontopodium alpinum extract
Thymus Vulgaris (Thyme) Extract
Buddleja Davidii Extract
Ethylhexylglycerin
Parfume

PURPOSE

wrinkle care

keep out of reach of the children

INDICATIONS AND USAGE

apply proper amount to the skin

WARNINGS

For external use only
When using this product

■ if the following symptoms occurs after use, stop use and consult with a skin specialist

red specks, swelling, itching

■ don’t use on the part where there is injury, eczema, or dermatitis

Keep out of reach of children

■ if swallowed, get medical help or contact a person control center immediately